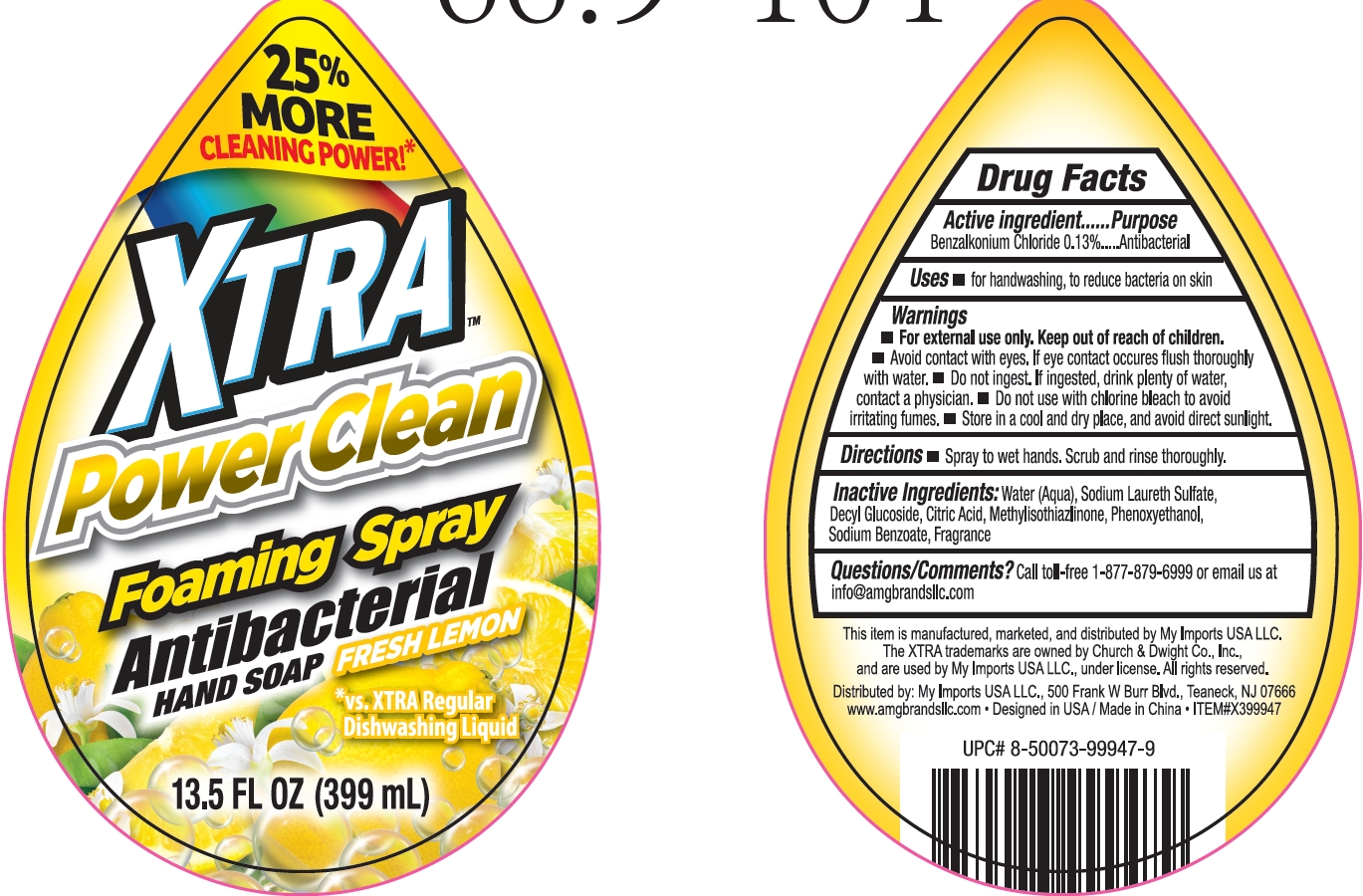 DRUG LABEL: XTRA Antibacterial Hand Fresh Lemon
NDC: 51628-4503 | Form: GEL
Manufacturer: MY IMPORTS USA LLC.
Category: otc | Type: HUMAN OTC DRUG LABEL
Date: 20250710

ACTIVE INGREDIENTS: BENZALKONIUM CHLORIDE 0.13 g/100 mL
INACTIVE INGREDIENTS: CITRIC ACID; PHENOXYETHANOL; METHYLISOTHIAZOLINONE; DECYL GLUCOSIDE; SODIUM BENZOATE; AQUA; SODIUM LAURETH SULFATE

XTRA Antibacterial Hand Soap Fresh Lemon

Active Ingredient

Benzalkonium Chloride 0.13%

Purpose

Antibacterial

Uses

For handwashing, to reduce bacteria on skin

Warnings

For external use only.

Keep out of reach of children

Keep out of reach od children

DO NOT USE

Avoid contact with eyes. If eye contact occures flush thoroughly with water.

Do not use with chlorine bleach to avoid irritating fumes.

ASK DOCTOR

Do not ingest. If ingested, drink plenty of water, contact a physician.

STORAGE AND HANDLING

Store in a cool and dry place, and avoid direct sunlight.

Directions

Spray to wet hands. scrub and rinse thoroughly.

Inactive ingredients

Water (Aqua)

Sodium Laureth Sulfate

Decyl Glucoside

Sodium Benzoate

Phenoxyethanol

Fragrance

Citric Acid

Methylisothiazlinone